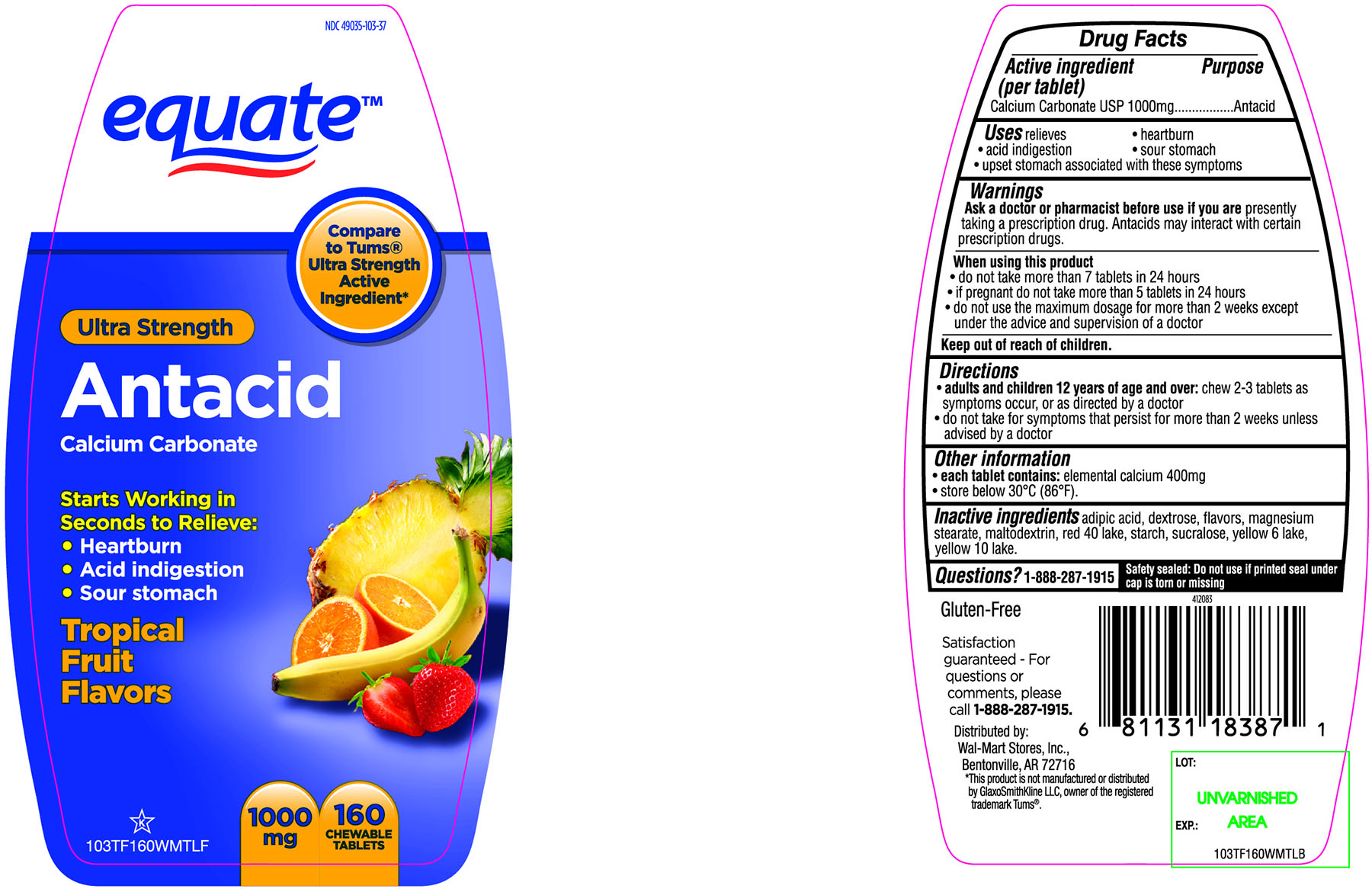 DRUG LABEL: equate Ultra Strength Antacid Calcium Carbonate
NDC: 49035-103 | Form: TABLET, CHEWABLE
Manufacturer: Wal-Mart Stores,Inc.,
Category: otc | Type: HUMAN OTC DRUG LABEL
Date: 20160321

ACTIVE INGREDIENTS: CALCIUM CARBONATE 1000 mg/1 1
INACTIVE INGREDIENTS: ADIPIC ACID; DEXTROSE; MAGNESIUM STEARATE; MALTODEXTRIN; FD&C RED NO. 40; STARCH, CORN; SUCRALOSE; FD&C YELLOW NO. 6; D&C YELLOW NO. 10

equate Ultra Strength Antacid Calcium Carbonate Chewable Tablets

Active ingredient (per tablet)

Calcium Carbonate USP 1000mg

Purpose

Antacid

Uses

relieves

- heartburn
- acid indigestion
- sour stomach
- upset stomach associated with these symptoms

Warnings

Ask a doctor or pharmacist before use if you are presentlytaking a prescription drug. Antacids may interact with certain prescription drugs.

When using this product

do not take more than 7 tablets in 24 hours
if pregnant do not take more than 5 tablets in 24 hours
do not use the maximum dosage for more than 2 weeks except under the advice and supervision of a doctor.

Directions

adults and children 12 years of age and over: chew 2-3 tablets as symptoms occur, or as directed by a doctor
do not take for symptoms that persist for more than 2 weeks unless advised by a doctor

Other information

each tablet contains: elemental calcium 400mg
store below 30°C (86°F).

Inactive ingredients

adipic acid, dextrose, flavors, magnesium stearate, maltodextrin, red 40 lake, starch, sucralose, yellow 6 lake, yellow 10 lake.

Questions?

1-888-287-1915

Safety sealed: Do not use if printed seal under cap is torn or missing

Package/Label Principal Display Panel

NDC 49035-103-37

equate™

Compare to Tums® Ultra Strength Active Ingredient*

Ultra Strength

Antacid

Calcium Carbonate

Starts Working in Seconds to Relieve:

- Heartburn
- Acid indigestion
- Sour stomach

Tropical Fruit Flavors

1000 mg

160 CHEWABLE TABLETS

Gluten- Free

Satisfaction guaranteed-

For questions or comments, please call

1-888-287-1915.

Distributed by: Wal-Mart Stores, Inc.,

Bentonville,AR 72716

*This product is not manufactured or distributed by GlaxoSmithKline LLC, owner of the registered trademark, Tums®.